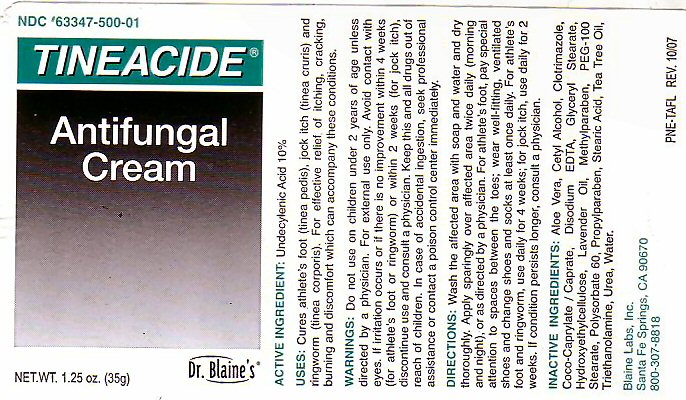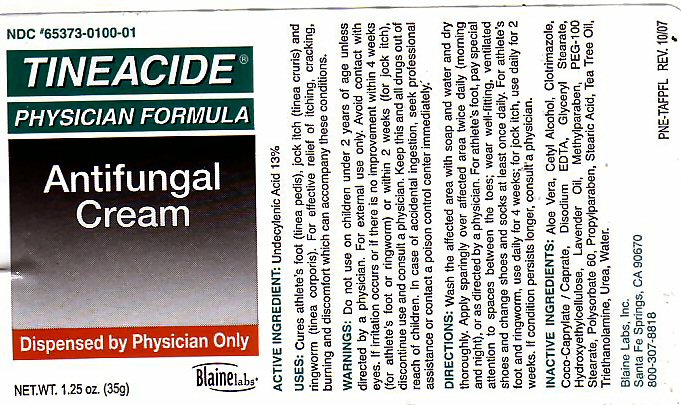 DRUG LABEL: Tineacide Physician Formula
NDC: 65373-100 | Form: CREAM
Manufacturer: Blaine Labs Inc.
Category: otc | Type: HUMAN OTC DRUG LABEL
Date: 20110121

ACTIVE INGREDIENTS: UNDECYLENIC ACID 13 g/100 g
INACTIVE INGREDIENTS: WATER; CETYL ALCOHOL; ALOE VERA LEAF; CLOTRIMAZOLE; EDETATE DISODIUM; GLYCERYL MONOSTEARATE; HYDROXYETHYL CELLULOSE (140 CPS AT 5%); ENGLISH LAVENDER OIL; METHYLPARABEN; POLYOXYL 100 STEARATE; POLYSORBATE 60; PROPYLPARABEN; STEARIC ACID; TEA TREE OIL; TROLAMINE; UREA

Active Ingredients

Undecylenic Acid

Inactive Ingredients

Aloe Vera, Cetyl Alcohol, Clotrimazole, Coco-Caprylate Caprate, Disodium EDTA, Glyceryl Stearate, Hydroxyethylcellulose, Lavender Oil, Methylparaben, PEG-100, Stearate, Polysorbate 60, Propylparaben, Stearic Acid, Tea Tree Oil, Triethanolamine, Urea, Water

Uses

Cures Athlete's Foot (tinea pedis) jock itch (tinea cruris) and ringworm (tinea corporis).

Uses

For effective relief of itching, cracking, burning and discomfort which can accompany these conditions.

Ask Your Physician

Do not use on children under 2 years of age unless directed by a physician

When Using This Product

Wash the affected area with soap and water and dry thoroughly. Apply sparingly over affected area twice daily (morning and night) or as directed by a physician. For athlete's foot pay special attention to spaces between the toes. wear well-fitting ventilated shoes and change shoes and socks at least once daily. For athlete's foot and ringworm use daily for 4 weeks. for jock itch use daily for 2 weeks. If condition persists longer, consult a physician.

Warnings

For external use only. Avoid contact with eyes. If irritation occurs or if there is no improvement within 4 weeks (for athlete's foot or ringworm) or within 2 weeks (for jock itch) discontinue use and consult a physician. Keep this and all drugs out of the reach of children. In case of accidental ingestion seek professional assistance or contact a poison control center immediately.

Tineacide Label

Tineacide Antifungal Cream Physician Formula
Dispensed by a physician only.